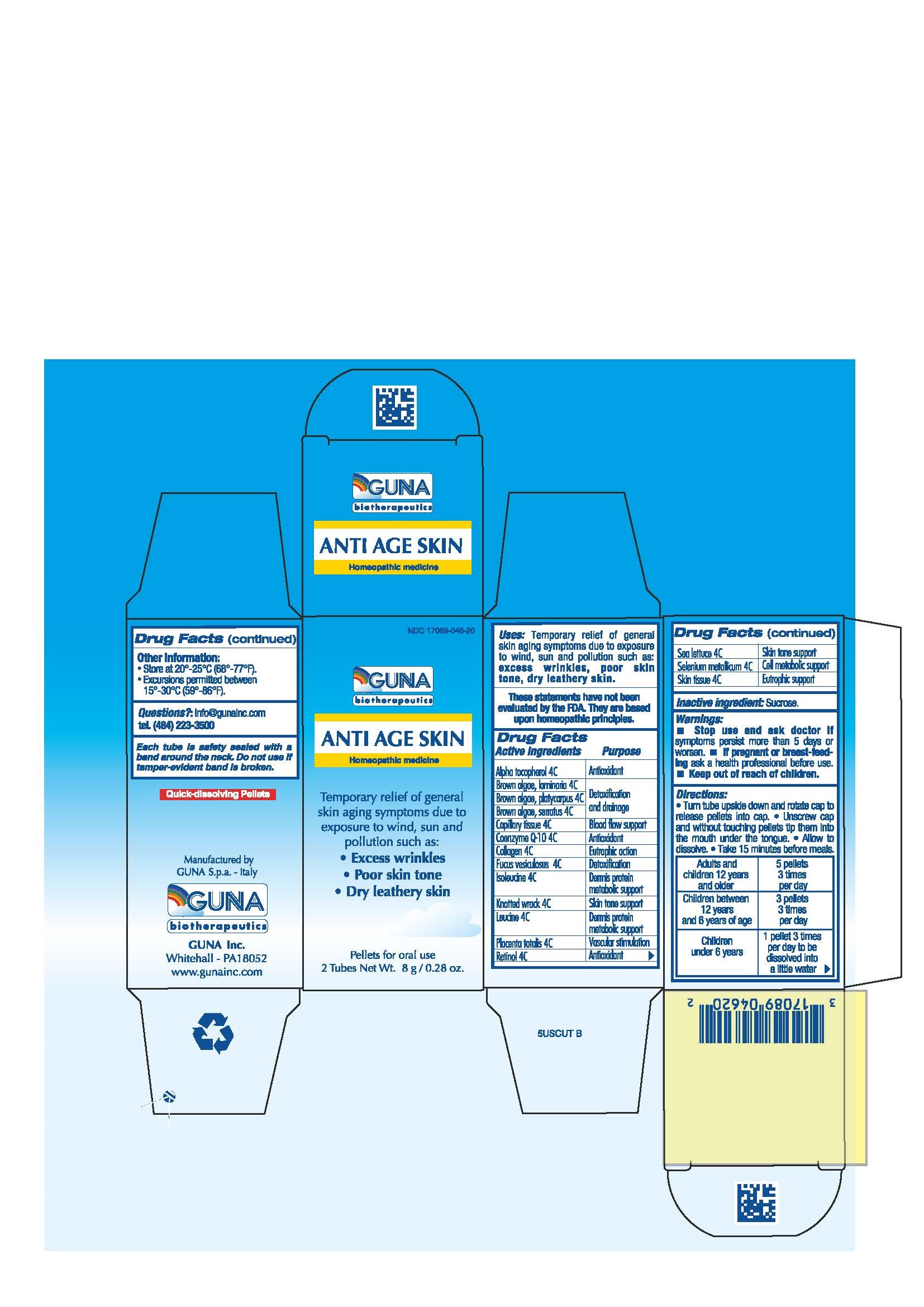 DRUG LABEL: ANTI AGE SKIN
NDC: 17089-046 | Form: PELLET
Manufacturer: Guna spa
Category: homeopathic | Type: HUMAN OTC DRUG LABEL
Date: 20181221

ACTIVE INGREDIENTS: ALPHA-TOCOPHEROL 4 [hp_C]/4 g; LAMINARIA DIGITATA 4 [hp_C]/4 g; BOTRYOGLOSSUM PLATYCARPUM 4 [hp_C]/4 g; FUCUS SERRATUS 4 [hp_C]/4 g; SUS SCROFA CAPILLARY TISSUE 4 [hp_C]/4 g; UBIDECARENONE 4 [hp_C]/4 g; SUS SCROFA COLLAGEN 4 [hp_C]/4 g; FUCUS VESICULOSUS 4 [hp_C]/4 g; ISOLEUCINE 4 [hp_C]/4 g; ASCOPHYLLUM NODOSUM 4 [hp_C]/4 g; LEUCINE 4 [hp_C]/4 g; SUS SCROFA PLACENTA 4 [hp_C]/4 g; RETINOL 4 [hp_C]/4 g; ULVA LACTUCA EXTRACT 4 [hp_C]/4 g; SELENIUM 4 [hp_C]/4 g; SUS SCROFA SKIN 4 [hp_C]/4 g
INACTIVE INGREDIENTS: SUCROSE 4 g/4 g

ANTI AGE SKIN

ACTIVE INGREDIENTS/PURPOSE

ALPHA TOCOPHEROL 4C ANTIOXIDANT
BROWN ALGAE, LAMINARIA 4C DETOXIFICATION AND DRAINAGE
BROWN ALGAE, PLATYCARPUS 4C DETOXIFICATION AND DRAINAGE
BROWN ALGAE, SERRATUS 4C DETOXIFICATION AND DRAINAGE
CAPILLARY TISSUE 4C BLOOD FLOW SUPPORT
COENZYME Q-10 4C ANTIOXIDANT
COLLAGEN 4C EUTROPHIC ACTION
FUCUS VESICULOSUS 4C DETOXIFICATION
ISOLEUCINE 4C DERMIS PROTEIN METABOLIC SUPPORT
KNOTTED WRACK 4C SKIN TONE SUPPORT
LEUCINE 4C DERMIS PROTEIN METABOLIC SUPPORT
PLACENTA TOTALIS 4C VASCULAR STIMULATION
RETINOL 4C ANTIOXIDANT
SEA LETTUCE 4C SKIN TONE
SELENIUM METALLICUM 4C CELL METABOLIC SUPPORT
SKIN TISSUE 4C EUTROPHIC SUPPORT

USES

For the temporary relief of general skin aging symptoms due to environmental exposure to wind, sun and pollution such as:

- Excess wrinkles
- Poor skin tone
- Dry leathery skin

WARNINGS

- Stop use and ask doctor if symptoms persist more than 5 days or worsen.
- If pregnant or breast-feeding ask a health professional before use.
- Keep out of reach of children.

PREGNANCY

If pregnant or breast-feeding ask a health professional before use.

WARNINGS

Keep this and all medicines out of reach of children

DIRECTIONS

Take 15 minutes before meals
Adults and children 12 years and older 5 pellets 3 times per day
Children between 12 years and 6 years of age 3 pellets 3 times per day
Children under 6 years 1 pellet 3 times per day to be dissolved into a little water

QUESTIONS

Questions?: info@gunainc.com
tel. (484) 223-3500

INDICATIONS AND USAGE

Turn tube upside down and rotate cap to release pellets into cap.
Unscrew cap and without touching pellets tip them into the mouth under the tongue.
Allow to dissolve
Take 15 minutes before meals.

- inactive ingredient: Sucorse.